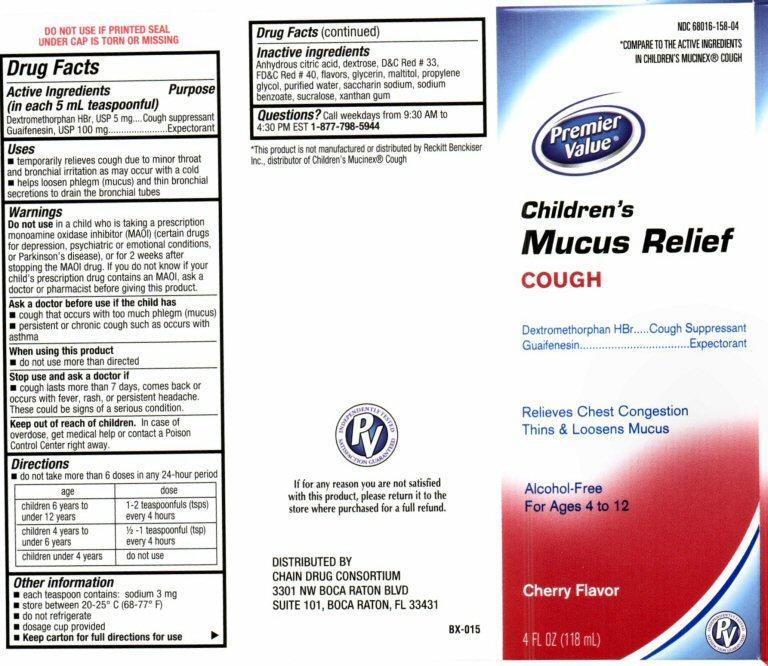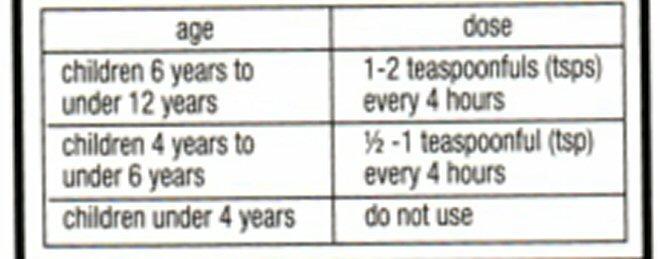 DRUG LABEL: Childrens Mucus Relief COUGH
NDC: 68016-158 | Form: LIQUID
Manufacturer: Chain Drug Consortium, LLC
Category: otc | Type: HUMAN OTC DRUG LABEL
Date: 20130401

ACTIVE INGREDIENTS: DEXTROMETHORPHAN HYDROBROMIDE 5 mg/5 mL; GUAIFENESIN 100 mg/5 mL
INACTIVE INGREDIENTS: ANHYDROUS CITRIC ACID; DEXTROSE; D&C RED NO. 33 ; FD&C RED NO. 40; GLYCERIN; MALTITOL; PROPYLENE GLYCOL; WATER; SACCHARIN SODIUM; SODIUM BENZOATE; SUCRALOSE; XANTHAN GUM

Active ingredients

Drug Facts
Active ingredients (in each 5 mL teaspoonful)
Dextromethorphan HBr 5 mg
Guaifenesin 100 mg

Purpose

Cough suppressant
Expectorant

Keep out of reach of children

In case of overdose, get medical help or contact a Poison Control center right away.

Uses

- temporarily relieves cough due to minor throat and bronchial irritation as may occur with a cold
- helps to loosen phlegm (mucus) and thin bronchial secretions to drain the bronchial tubes

Warnings

Do not use

in a child who is taking a prescription monoamine oxidase inhibitor (MAOI) (certain drugs for depression, psychiatric or emotional conditions, or Parkinson’s disease), or for two weeks after stopping the MAOI drug. If you do not know if your child’s prescription drug contains an MAOI, ask a doctor or a pharmacist before taking this product.

Ask a doctor before use if the child has

- cough that occurs with too much phlegm (mucus)
- persistent or chronic cough such as occurs with asthma

When using this product

- do not use more than directed

Stop use and ask a doctor if

- cough lasts more than 7 days, comes back or occurs with fever, rash, or persistent headache.
- These could be signs of a serious condition.

Directions

- do not take more than 6 doses in any 24-hour period

Other information

each teaspoon contains: sodium 3 mg

- store between 20-25 ° C (68-77° F)
- do not refrigerate
- dosage cup provided
- Keep carton for full directions for use

Inactive ingredients

citric acid anhydrous, dextrose, D and C Red # 33, FD and C Red # 40, flavors, glycerin, maltitol, propylene glycol, purified water, saccharin sodium, sodium benzoate, sucralose, Xanthan gum

Questions?

Call weekdays from 9:30 AM to 4:30 PM EST

1-877-798-5944

Product Label

NDC 68016-158-04
*COMPARE TO THE ACTIVE INGREDIENTS IN CHILDRENS MUCINEX® COUGH
Premier Value®
Childrens
Mucus Relief
COUGH

Dextromethorphan HBr ..... Cough Suppressant
Guaifenesin ..................... Expectorant
Relieves Chest Congestion
Thins and Loosens Mucus
Alcohol Free
For Ages 4 to 12

Cherry Flavor

4 FL OZ (118mL)
INDEPENDENTLY TESTED SATISFACTION GUARANTEED PV
DO NOT USE IF PRINTED SEAL UNDER CAP IS TORN OR MISSING
*This product is not manufactured or distributed by Reckitt Benckiser Inc. distributor of Mucinex® Cough
If for Any reason you are not satisfied with this product, please return it to the store where purchased for a full refund.
DISTRIBUTED BY
CHAIN DRUG CONSORTIUM
3301 NW BOCA RATON BLVD
SUITE 101, BOCA RATON, FL 33431
BX-015